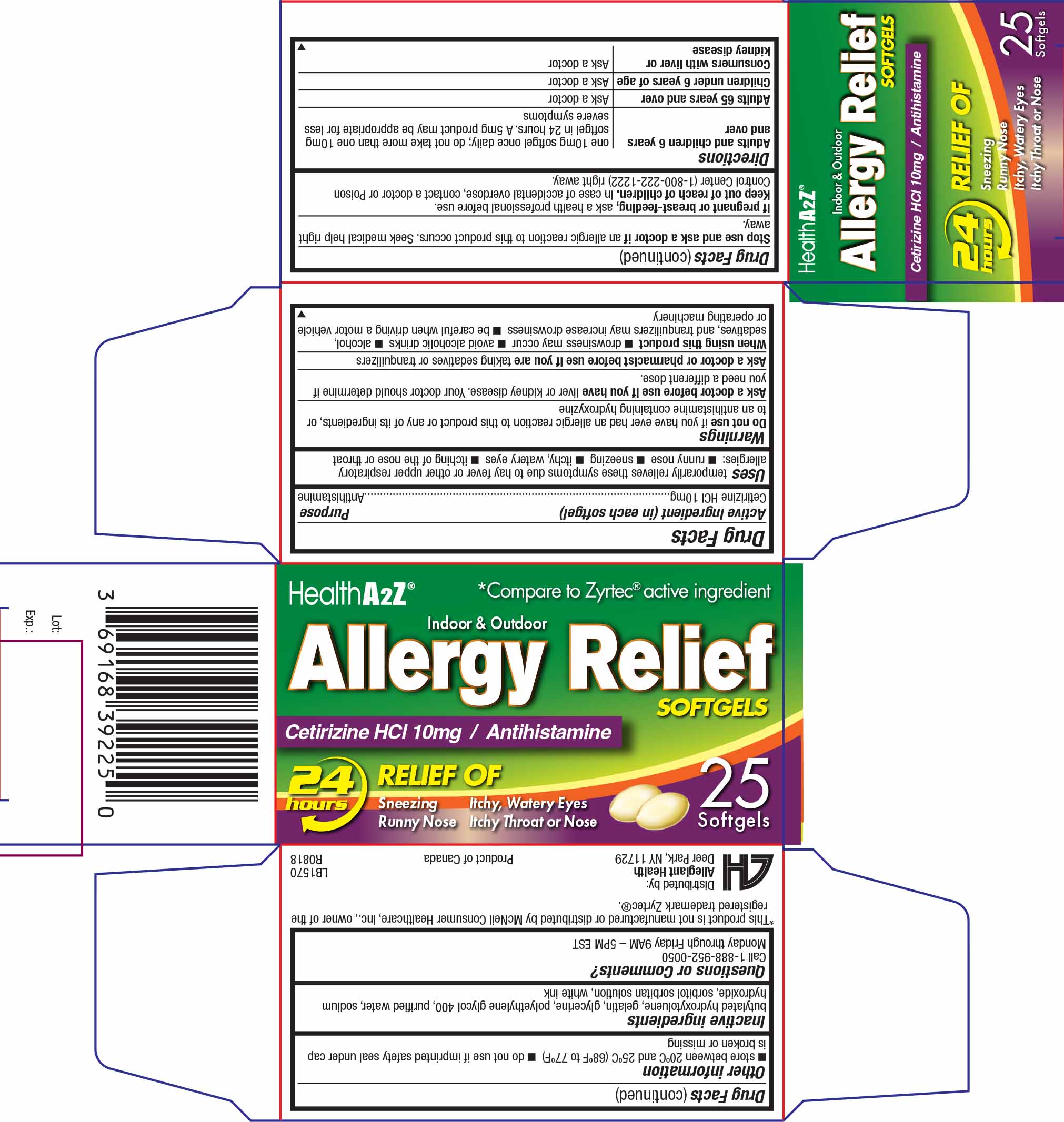 DRUG LABEL: Allergy Relief
NDC: 69168-392 | Form: CAPSULE, LIQUID FILLED
Manufacturer: Allegiant Health
Category: otc | Type: HUMAN OTC DRUG LABEL
Date: 20181231

ACTIVE INGREDIENTS: CETIRIZINE HYDROCHLORIDE 10 mg/1 1
INACTIVE INGREDIENTS: BUTYLATED HYDROXYTOLUENE; GELATIN; GLYCERIN; POLYETHYLENE GLYCOL 400; SODIUM HYDROXIDE

Drug Facts

Active ingredient (in each softgel)

Cetirizine HCl 10 mg

Purpose

Antihistamine

Uses

temporarily relieves these symptoms due to hay fever or other upper respiratory allergies:

- runny nose
- sneezing
- itchy, watery eyes
- itching of the nose or throat

Warnings

Do not use if you have ever had an allergic reaction to this product or any of its ingredients or to an antihistamine containing hydroxyzine

Ask a doctor before use if you have

liver or kidney disease. Your doctor should determine if you need a different dose.

Ask doctor or pharmacist before use if you are

taking sedatives or tranquilizers

When using this product

- drowsiness may occur
- avoid alcoholic drinks
- alcohol, sedatives, and tranquilizers may increase drowsiness
- be careful when drivinga motor vehicle or operating machinery

Stop use and ask doctor

if an allergic reaction to this product occurs. Seek medical help right away.

If pregnant or breast-feeding, ask a health professional before use.

Keep Out of Reach of Children

In case of accidental overdose, contact a doctor or Poison Control Center (1-800-222-1222) right away.

Directions

- Adults and children 6 years and over: one 10mg tablet once daily; do not take more than one 10mg tablet in 24 hours. A 5mg product may be appropriate for less severe symptoms
- Adults 65 years and over: ask a doctor
- Children under 6 years of age: ask a doctor
- Consumers with liver or kidney disease: ask a doctor

Other information

- store between 20°C to 25°C (68°F to 77°F)
- do not use if imprinted safety seal under cap is broken or missing

Inactive Ingredients

butylated hydroxytoluene, gelatin, glycerine, polyethylene glycol 400, purified water, sodium hydroxide, sorbitol sorbitan solution, white ink

Questions or Comments?

Call 1-888-952-0050

Monday through Friday 9AM – 5PM EST

Manufactured for

A&Z Pharmaceutical, Inc.
Hauppauge, NY 11788

Package/Label Principal Display Panel

Cetirizine HCl 10mg Softgels